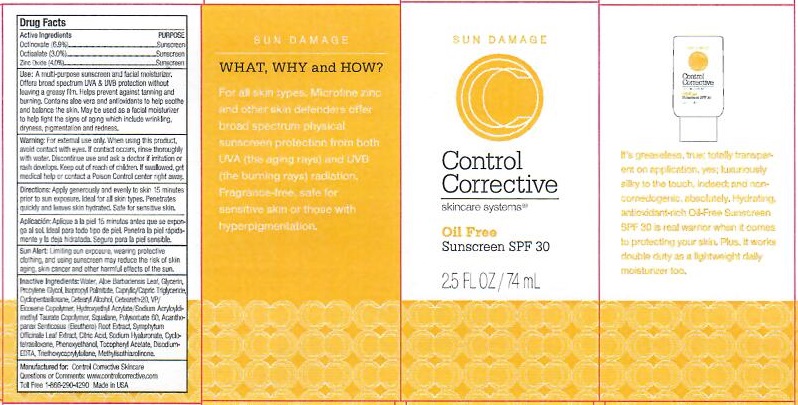 DRUG LABEL: CONTROL CORRECTIVE SUNSCREEN
NDC: 70764-204 | Form: CREAM
Manufacturer: CONTROL CORRECTIVE SKINCARE INC
Category: otc | Type: HUMAN OTC DRUG LABEL
Date: 20251231

ACTIVE INGREDIENTS: OCTINOXATE 6.9 g/100 mL; OCTISALATE 3 g/100 mL; ZINC OXIDE 4 g/100 mL
INACTIVE INGREDIENTS: WATER; ALOE VERA LEAF; GLYCERIN; PROPYLENE GLYCOL; ISOPROPYL PALMITATE; MEDIUM-CHAIN TRIGLYCERIDES; CYCLOMETHICONE 5; CETOSTEARYL ALCOHOL; POLYOXYL 20 CETOSTEARYL ETHER; VINYLPYRROLIDONE/EICOSENE COPOLYMER; HYDROXYETHYL ACRYLATE/SODIUM ACRYLOYLDIMETHYL TAURATE COPOLYMER (45000 MPA.S AT 1%); SQUALANE; POLYSORBATE 60; ELEUTHERO; COMFREY LEAF; ANHYDROUS CITRIC ACID; HYALURONATE SODIUM; CYCLOMETHICONE 4; PHENOXYETHANOL; .ALPHA.-TOCOPHEROL ACETATE; EDETATE DISODIUM; TRIETHOXYCAPRYLYLSILANE; METHYLISOTHIAZOLINONE

CONTROL CORRECTIVE - OIL FREE SUNSCREEN SPF-30 (70764-204)

ACTIVE INGREDIENTS

OCTINOXATE (6.9%)

OCTISALATE (3.0%)

ZINC OXIDE (4.0%)

PURPOSE

SUNSCREEN

USE

A MULTI-PURPOSE SUNSCREEN AND FACIAL MOISTURIZER. OFFERS BROAD SPECTRUM UVA & UVB PROTECTION WITHOUT LEAVING A GREASY FILM. HELPS PREVENT AGAINST TANNING AND BURNING. CONTAINS ALOE VERA AND ANTIOXIDANTS TO HELP SOOTHE AND BALANCE THE SKIN. MAY BE USED AS A FACIAL MOISTURIZER TO HELP FIGHT THE SIGNS OF AGING WHICH INCLUDES WRNKLING, DRYNESS, PIGMENTATION AND REDNESS.

WARNING

FOR EXTERNAL USE ONLY. WHEN USING THIS PRODUCT, AVOID CONTACT WITH EYES. IF CONTACT OCCURS, RINSE THOROUGHLY WITH WATER. DISCONTINUE USE AND ASK A DOCTOR IF IRRITATION OR RASH DEVELOPS.

DIRECTIONS

APPLY GENEROUSLY AND EVENLY TO SKIN 15 MINUTES PRIOR TO SUN EXPOSURE. IDEAL FOR ALL SKIN TYPES. PENETRATES QUICKLY AND LEAVES SKIN HYDRATED. SAFE FOR SENSITIVE SKIN.

OTHER SAFETY INFORMATION

SUN ALERT: LIMITING SUN EXPOSURE, WEARING PROTECTIVE CLOTHING, AND USING SUNSCREEN MAY REDUCE THE RISK OF SKIN AGING, SKIN CANCER, AND OTHER HARMFUL EFFECTS OF THE SUN.

INACTIVE INGREDIENTS

WATER, ALOE BARBADENSIS LEAF, GLYCERIN, PROPYLENE GLYCOL, ISOPROPYL PALMITATE, CAPRYLIC/CAPRIC TRIGLYCERIDES, CYCLOPENTASILOXANE, CETEARYL ALCOHOL, CETEARETH-20, VP/EICOSENE COPOLYMER, HYDROXYETHYL ACRYLATE/SODIUM ACRYLOYLDIMETHYL TAURATE COPOLYMER, SQUALANE, POLYSORBATE 60, ACANTHOPANAX SENTICOSUS (ELEUTHERO) ROOT EXTRACT, SYMPHYTUM OFFICINALE LEAF EXTRACT, CITRIC ACID, SODIUM HYALURONATE, CYCLOTETRASILOXANE, PHENOXYETHANOL, TOCOPHERYL ACETATE, TRIETHOXYCAPRYLYLSILANE, METHYLISOTHIAZOLINONE

KEEP OUT OF REACH OF CHILDREN. IF SWALLOWED, GET MEDICAL HELP OR CONTACT A POISON CONTROL CENTER RIGHT AWAY.

QUESTIONS OR COMMENTS

WWW.CONTROLCORRECTIVE.COM

TOLL FREE 1-866-290-4290 MADE IN USA